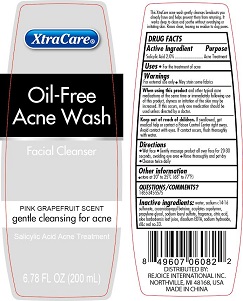 DRUG LABEL: Acne wash facial cleanser pink grapefruit
NDC: 57337-080 | Form: LIQUID
Manufacturer: Rejoice International Corp
Category: otc | Type: HUMAN OTC DRUG LABEL
Date: 20250206

ACTIVE INGREDIENTS: SALICYLIC ACID 2 g/200 mL
INACTIVE INGREDIENTS: D&C RED NO. 33; WATER; GLYCERIN; COCAMIDOPROPYL BETAINE; SODIUM C14-16 OLEFIN SULFONATE; PROPYLENE GLYCOL; SODIUM LAURYL SULFATE; CITRIC ACID MONOHYDRATE; ALOE VERA LEAF; DISODIUM EDTA-COPPER; SODIUM HYDROXIDE

Acne wash facial cleanser pink grapefruit

Purpose

Acne treatment

Active Ingredient

Salicylic Acid 2%

USAGE

For the treatments of acne

Directions

Wet face

Gently massage product all over face for 20-30 seconds, avoiding eye area

Rinse thoroughly and pat dry

Cleanse twice a day.

Keep out of reach of children

If swallowed get medical help or contact a poison control center right away.

Avoid contact with eyes. If this occurs, flush thoroughly with water.

INACTIVE INGREDIENT

WATER, SODIUM C14-16 SULFONATE, COCAMIDOPROPYL BETAINE, ACRYLATES COPOLYMER, PROPYLENE GLYCOL, SODIUM LAURYL SULFATE, FRAGRANCE, CITRIC ACID, ALOE BARBADENSIS LEAF JUICE, DISODIUM EDTA, SODIUM HYDROXIDE, D&C RED NO.33.

Warnings

For external use only May stain some fabrics.
When using this product and other typical acne medications at the same time or immediately following use of this product, dryness or irritation of the skin may be increased. If this occurs, only one medication should be used unless directed by a doctor